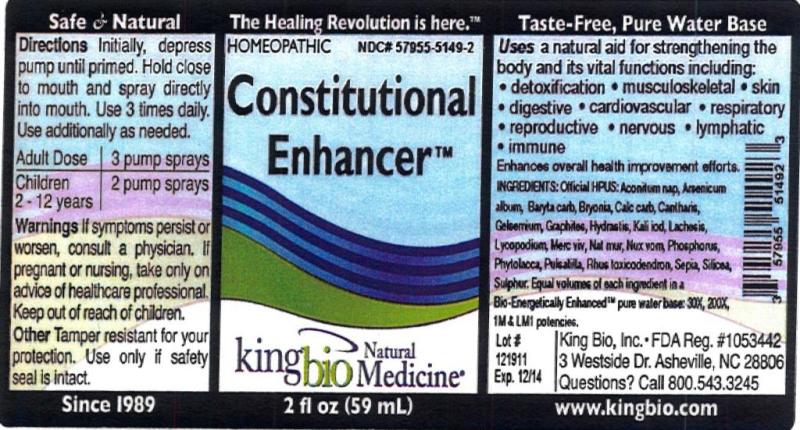 DRUG LABEL: Constitutional Enhancer
NDC: 57955-5149 | Form: LIQUID
Manufacturer: King Bio Inc.
Category: homeopathic | Type: HUMAN OTC DRUG LABEL
Date: 20120402

ACTIVE INGREDIENTS: ACONITUM NAPELLUS 30 [hp_X]/59 mL; ARSENIC TRIOXIDE 30 [hp_X]/59 mL; BARIUM CARBONATE 30 [hp_X]/59 mL; BRYONIA ALBA ROOT 30 [hp_X]/59 mL; OYSTER SHELL CALCIUM CARBONATE, CRUDE 30 [hp_X]/59 mL; LYTTA VESICATORIA 30 [hp_X]/59 mL; GELSEMIUM SEMPERVIRENS ROOT 30 [hp_X]/59 mL; GRAPHITE 30 [hp_X]/59 mL; GOLDENSEAL 30 [hp_X]/59 mL; POTASSIUM IODIDE 30 [hp_X]/59 mL; LACHESIS MUTA VENOM 30 [hp_X]/59 mL; LYCOPODIUM CLAVATUM SPORE 30 [hp_X]/59 mL; MERCURY 30 [hp_X]/59 mL; SODIUM CHLORIDE 30 [hp_X]/59 mL; STRYCHNOS NUX-VOMICA SEED 30 [hp_X]/59 mL; PHYTOLACCA AMERICANA ROOT 30 [hp_X]/59 mL; PULSATILLA VULGARIS 30 [hp_X]/59 mL; TOXICODENDRON PUBESCENS LEAF 30 [hp_X]/59 mL; SEPIA OFFICINALIS JUICE 30 [hp_X]/59 mL; SILICON DIOXIDE 30 [hp_X]/59 mL; SULFUR 30 [hp_X]/59 mL; PHOSPHORUS 30 [hp_X]/59 mL
INACTIVE INGREDIENTS: WATER

Constitutional Enhancer

Active Ingredients

Official HPUS: Aconitum napellus, Arsenicum album, Baryta carbonica, Cantharis, Gelsemium sempervirens, Graphites, Hydrastis canadensis, Kali iodatum, Lachesis mutus, Lycopodium clavatum, Mercurius vivus, Natrum muriaticum, Nux vomica, Phosphorus, Phytolacca decandra, Pulsatilla, Rhus toxicodendron, Sepia, Silicea and Sulphur.

Reference image constitutional.jpg

Inactive Ingredient

Equal volumes of each ingredient in a Bio-Energetically Enhanced pure water base: 30X, 200X, 1M and LM1 potencies.

Reference image constitutional.jpg

Purpose

Uses a natural aid for strengthening the body and its vital functions including:

- detoxification
- musculoskeletal
- skin
- digestive
- cardiovascular
- respiratory
- reproductive
- nervous
- lymphatic
- immune

Enhances overall health improvement efforts.
Reference image constitutional.jpg

Directions

Initially, depress pump until primed. Hold close to mouth and spray directly into mouth. Use 3 times daily. Use additionally as needed.

Adult Dose 3 pump sprays

Children 2-12 years 2 pump sprays

Reference image constitutional.jpg

Warnings

If symptoms persist or worsen, consult a physician. If pregnant or nursing, take only on advice of healthcare professional. Keep out of reach of children.

Other: Tamper resistant for your protection. Use only if safety seal is intact.

Reference image constitutional.jpg

Keep out of reach of children.

Reference image constitutional.jpg

Indications and Usage

Uses a natural aid for strengthening the body and its vital function including: detoxification, musculoskeletal, skin, digestive, cardiovascular, respiratory, reproductive, nervous, lymphatic and immune. Enhances overall health improvement efforts.

Reference image constitutional.jpg

PACKAGE LABEL

King Bio Inc.

3 Westside Drive

Asheville, NC 28806

Questions? Call 800.543.3245

www.kingbio.com